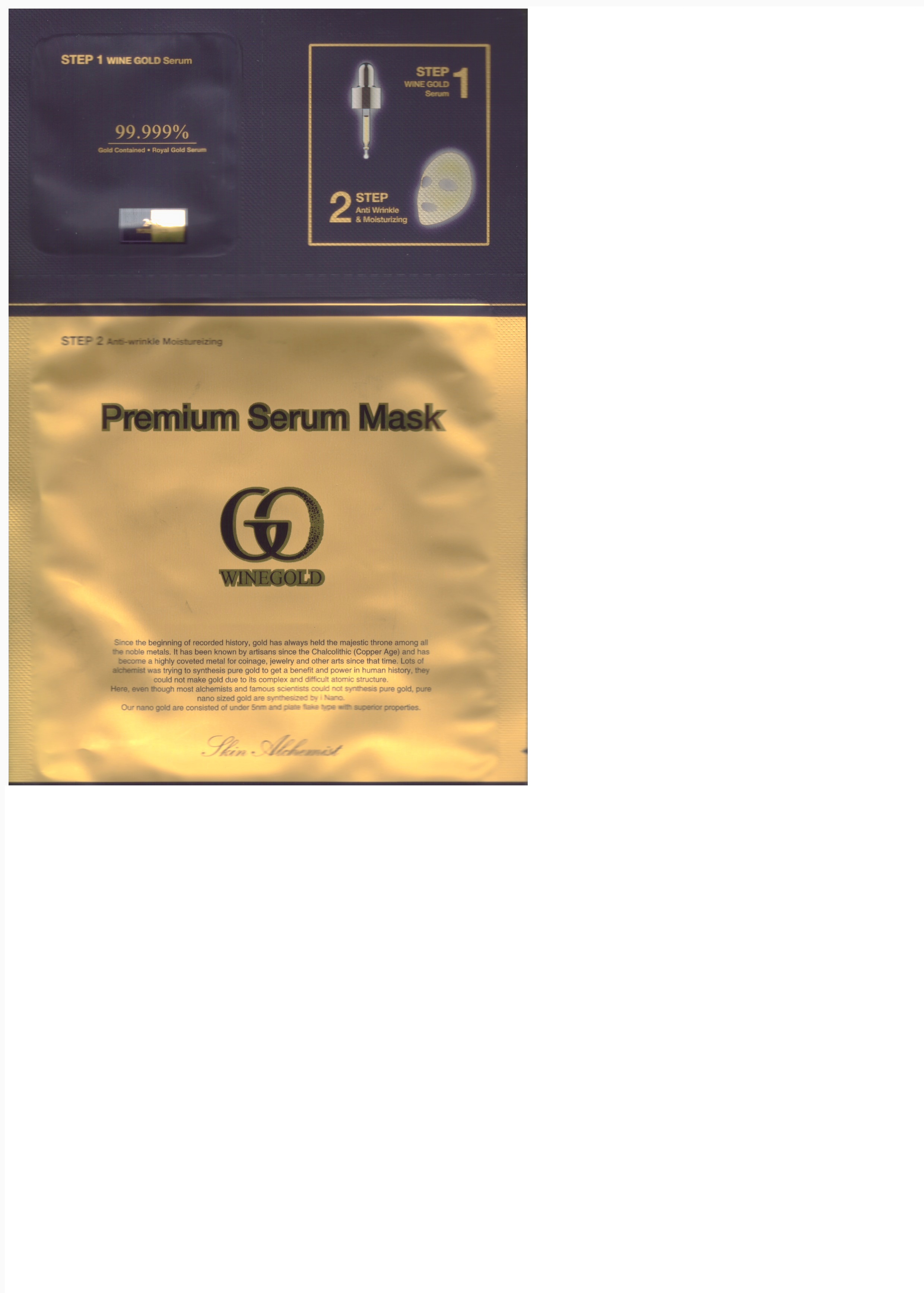 DRUG LABEL: Premiu Serum Mask
NDC: 72160-0001 | Form: LIQUID
Manufacturer: iNANO Co., Ltd.
Category: otc | Type: HUMAN OTC DRUG LABEL
Date: 20180311

ACTIVE INGREDIENTS: GLYCERIN 5 g/100 g
INACTIVE INGREDIENTS: WATER

ACTIVE INGREDIENT

glycerin

INACTIVE INGREDIENT

water, niacinamide, hydrogenated polydecene, hexyl laurate, angelica gigas root extract, etc

PURPOSE

whitening, anti wrinkle

WARNINGS

1. If the following symptoms occur after product use, stop using the product immediately and consult a dermatologist (continuous use can exacerbate the symptoms).
1) Occurrence of red spots, swelling, itchiness, and other skin irritation
2) If the symptoms above occur after the application area is exposed to direct sunlight

2. Do not use on open wounds, eczema, and other skin irritations
3. Precaution for Storage and Handling
- Keep out of reach of infants and children
- Do not to store in a place with high/low temperature and exposed to direct sunlight

Keep out of reach of children.

INDICATIONS AND USAGE

1. after washing, remove moisture entirely to arrange skin texture

2. apply the wine gold serum (step 1) onto the face equaly and rub the serum softly like massae to absorb perfectly

3. unfolding the mask (step 2), position the mask on the fact according to position of eyes and mouth

4. remove the mask sheet after 15~30 minutes, after that softly pat any remaining essence into skin like massage

DOSAGE AND ADMINISTRATION

for external use only